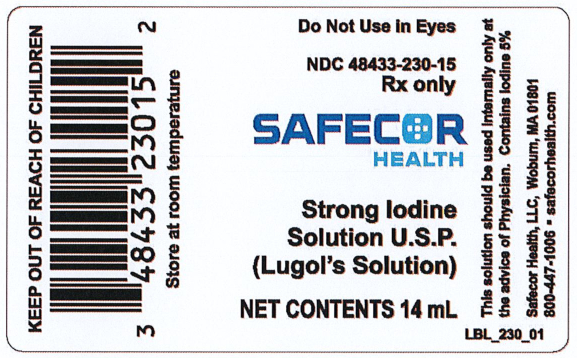 DRUG LABEL: Strong Iodine Solution
NDC: 48433-230 | Form: SOLUTION/ DROPS
Manufacturer: Safecor Health, LLC
Category: prescription | Type: HUMAN PRESCRIPTION DRUG LABEL
Date: 20250108

ACTIVE INGREDIENTS: IODINE 700 mg/1 mL; POTASSIUM IODIDE 1400 mg/1 mL
INACTIVE INGREDIENTS: WATER

NDC 48433-230-15
STRONG IODINE SOLUTION, U.S.P.
(Lugol's Solution)

DESCRIPTION

Iodine 5g, potassium iodide 10g, in enough purified water to make 100 ml.

INDICATIONS

Strong Iodine Solution, containing 5 percent of iodine and 10 percent of potassium iodide, is employed in the prophylaxis of simple and colloid goiters and in the treatment of exophthalmic goiter. It can be used alone as a preoperative preparation but is now most commonly used concomitantly with propylthiouracil and other antithyroid drugs. When used with these drugs, Strong Iodine Solution produces involution of the hyperplastic gland thus making a less triable and vascular gland for thyroidectomy. In addition, it has an additive antithyroid action that helps make the patient enthyroid faster than if the antithyroid drugs were used alone.

CONTRAINDICATIONS

The use of iodides may be contraindicated in patients with tuberculosis because it is believed they may cause a breakdown of healing lesions. The use of iodides is contraindicated in patients with iododerma, laryngeal edema, and swelling of salivary glands or increased salivation upon previous exposure to iodides. Strong Iodine Solution is ineffective in the treatment of postoperative thyroid crisis.

PRECAUTIONS

Iodine therapy does not completely control the manifestations of hyperthyroidism and after a variable period of time, the beneficial effects wear off. With continued administration of the drug, the hyperthyroidism may return in its initial intensity or become even more severe than it was at first. Measurements of the protein-bound iodine or of the uptake of radioiodine are rendered useless if iodine is given.

WARNINGS

Prolonged therapy may cause iodism. USE IN PREGNANCY: The drug readily crosses the placental barrier and may affect the fetus if used during pregnancy.

ADVERSE REACTIONS

Ingestion of large quantities of Strong Iodine Solution may cause abdominal pain, nausea, vomiting and diarrhea. Average doses may cause skin rash.

DOSAGE

Strong Iodine Solution is for oral use only. The usual dosage of Strong Iodine Solution is 2 to 6 drops (0.1 to 0.3 ml) three times daily taken in water after meals for two or three weeks prior to operation. In thyroid crisis the dosage is 1 ml three times a day.

HOW SUPPLIED

Bottles of 14 ml, amber glass with lined plastic closures. Accompanying each bottle is a glass dropper which should be used when the solution is ready to be dispensed to minimize any loss of free iodine through the bulb of the dropper.

STORAGE

Store at room temperature

Rx only

SAFECOR HEALTH, LLC
WOBURN, MA 01801

230-02
Rev 05/2019

———Principal Display Panel———

Do Not Use in Eyes

NDC 48433-230-15
Rx only

SAFECOR
HEALTH

Strong Iodine
Solution U.S.P.
(Lugol's Solution)

NET CONTENTS 14 mL